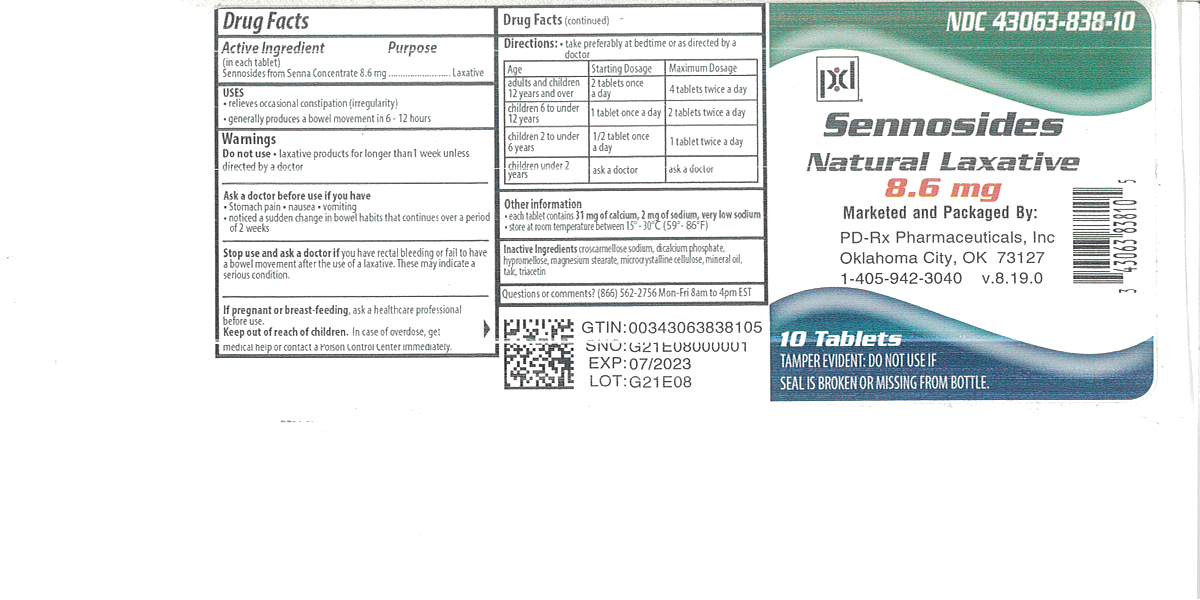 DRUG LABEL: Senna Laxative
NDC: 43063-838 | Form: TABLET, FILM COATED
Manufacturer: PD-Rx Pharmaceuticals, Inc.
Category: otc | Type: HUMAN OTC DRUG LABEL
Date: 20250521

ACTIVE INGREDIENTS: SENNOSIDES A AND B 8.6 mg/1 1
INACTIVE INGREDIENTS: CROSCARMELLOSE SODIUM; CALCIUM PHOSPHATE, DIBASIC, ANHYDROUS; HYPROMELLOSES; MAGNESIUM STEARATE; CELLULOSE, MICROCRYSTALLINE; MINERAL OIL

Drug Facts

Active ingredient (in each tablet)

Sennosides 8.6mg

Purpose

Laxative

Uses

- relieves occasional constipation (irregularity)
- this product generally produces a bowel movement in 6 to 12 hours

Warnings

Do not use

for more than one week unless directed by a doctor

Ask a doctor before use if you

- have abdominal pain, nausea, or vomiting
- are taking mineral oil
- noticed a sudden change in bowel habits that last over 2 weeks

Stop use and ask a doctor if

- you have no bowel movement within 12 hours
- you have rectal bleeding

These could be signs of a serious condition

If pregnant or breast-feeding,

ask a health professional before use.

Keep out of reach of children.

In case of overdose, get medical help or contact a Poison Control Center right away.

Directions

- do not exceed recommended dose

Age | Starting Dose | Maximum Dose
adults and children 12 years of age and older | 2 tablets once a day preferably at bedtime; increase if needed, or as directed by a doctor | 4 tablets twice a day, in the morning and at bedtime
children under 12 years | ask a doctor | ask a doctor

Other information

- Tamper Evident: Do not use if safety seal is broken or missing from bottle.
- each tablet contains: calcium 20 mg, potassium 70 mg
- store at room temperature

Inactive ingredients:

croscarmellose sodium, dicalcium phosphate, hypromellose, magnesium stearate, microcrystalline cellulose, mineral oil

Questions?

Adverse drug event call: (866) 562-2756

16 HOW SUPPLIED

Senna Laxative Tablets are available as follows:

8.6 mg: Brown, round, scored tablet, debossed “SB”. Available in bottles of

10 tablets (NDC 43063-838-10)

30 tablets (NDC 43063-838-30)